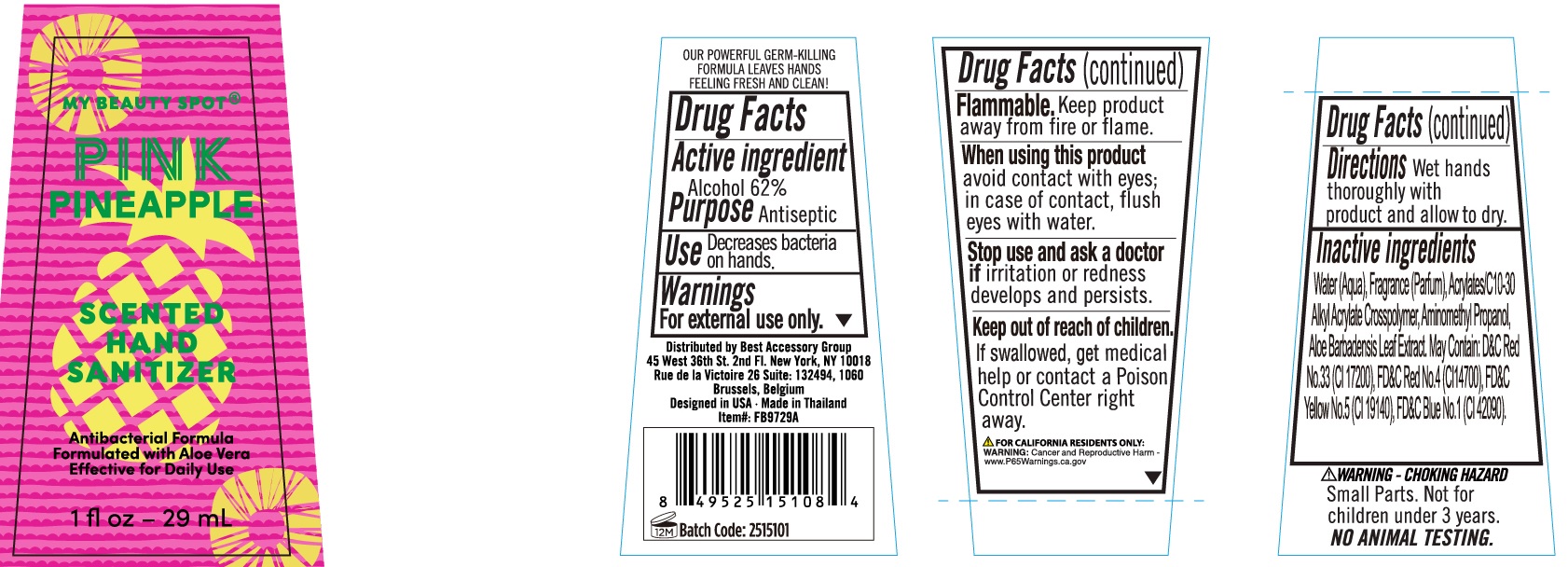 DRUG LABEL: Pink Pineapple SCENTED HAND SANITIZER
NDC: 85588-201 | Form: GEL
Manufacturer: MELON BIO-TECH (THAILAND) CO., LTD.
Category: otc | Type: HUMAN OTC DRUG LABEL
Date: 20250428

ACTIVE INGREDIENTS: ALCOHOL 62 mL/100 mL
INACTIVE INGREDIENTS: WATER; ALOE BARBADENSIS LEAF JUICE; CARBOMER COPOLYMER TYPE A; AMINOMETHYLPROPANOL

Scented Hand Sanitizer

Active ingredient

Alcohol 62%

Purpose

Antiseptic

Use

Decrease bacteria on hands.

Warnings

For external use only.

Flammable.Keep product away from fire or flame.

When using this product

avoid contact with eyes; in case of contact, flush eyes with water.

Stop use and ask a doctor if

irritation or redness develops and persists.

Keep out of reach of children.

If swallowed, get medical help or contact a Poison Control Center right away.

Directions

Wet hands thoroughly with product and allow to dry.

Inactive ingredients

Water (Aqua), ACRYLATES/C10-30 ALKYL ACRYLATE CROSSCOPOLYMER, AMINOMETHYL PROPANOL, Fragrance (Parfum), May contain: D&C Red No. 33 (Cl 17200), FD&C Red No. 4 (Cl 14700), FD&C Yellow No. 5 (Cl 19140), FD&C Blue No. 1 (Cl 42090).

warning - choking hazard

small parts. not for children under 3 years.

No Animal Testing